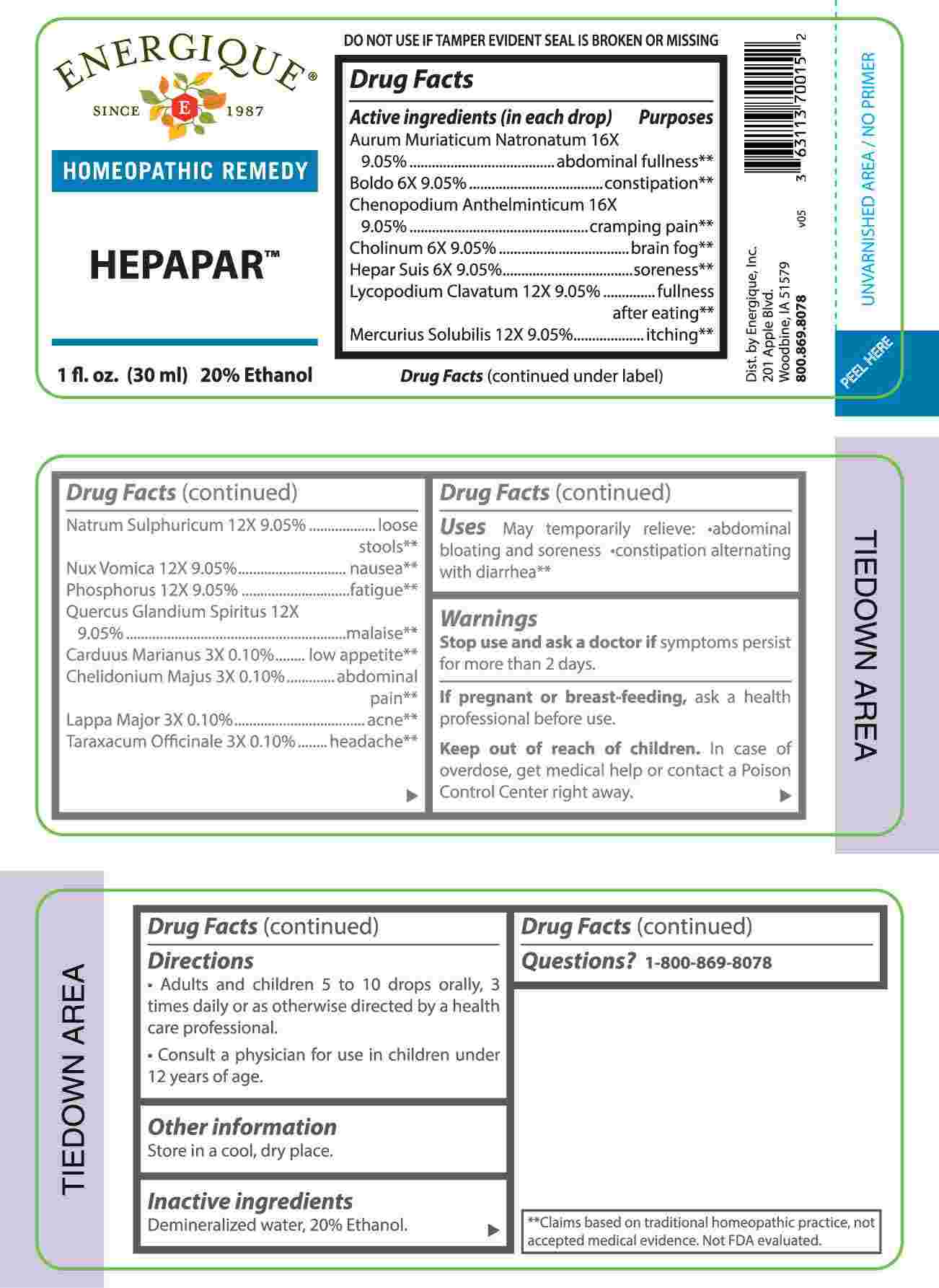 DRUG LABEL: Hepapar
NDC: 44911-0719 | Form: LIQUID
Manufacturer: Energique, Inc.
Category: homeopathic | Type: HUMAN OTC DRUG LABEL
Date: 20240826

ACTIVE INGREDIENTS: MILK THISTLE 3 [hp_X]/1 mL; CHELIDONIUM MAJUS WHOLE 3 [hp_X]/1 mL; ARCTIUM LAPPA ROOT 3 [hp_X]/1 mL; TARAXACUM OFFICINALE 3 [hp_X]/1 mL; PEUMUS BOLDUS LEAF 6 [hp_X]/1 mL; CHOLINE HYDROXIDE 6 [hp_X]/1 mL; PORK LIVER 6 [hp_X]/1 mL; LYCOPODIUM CLAVATUM SPORE 12 [hp_X]/1 mL; MERCURIUS SOLUBILIS 12 [hp_X]/1 mL; SODIUM SULFATE 12 [hp_X]/1 mL; STRYCHNOS NUX-VOMICA SEED 12 [hp_X]/1 mL; PHOSPHORUS 12 [hp_X]/1 mL; QUERCUS ROBUR NUT 12 [hp_X]/1 mL; SODIUM TETRACHLOROAURATE 16 [hp_X]/1 mL; DYSPHANIA AMBROSIOIDES WHOLE 16 [hp_X]/1 mL
INACTIVE INGREDIENTS: WATER; ALCOHOL

DRUG FACTS:

ACTIVE INGREDIENTS:

(in each drop) Aurum Muriaticum Natronatum 16X 9.05%, Boldo 6X 9.05%, Chenopodium Anthelminticum 16X 9.05%, Cholinum 6X 9.05%, Hepar Suis 6X 9.05%, Lycopodium Clavatum 12X 9.05%, Mercurius Solubilis 12X 9.05%, Natrum Sulphuricum 12X 9.05%, Nux Vomica 12X 9.05%, Phosphorus 12X 9.05%, Quercus Glandium Spiritus 12X 9.05%, Carduus Marianus 3X 0.10%, Chelidonium Majus 3X 0.10%, Lappa Major 3X 0.10%, Taraxacum Officinale 3X 0.10%.

PURPOSE:

Aurum Muriaticum Natronatum – abdominal fullness,** Boldo - constipation,** Chenopodium Anthelminticum – cramping pain,** Cholinum – brain fog,** Hepar Suis - soreness,** Lycopodium Clavatum – fullness after eating,** Mercurius Solubilis - itching,** Natrum Sulphuricum – loose stools,** Nux Vomica - nausea,** Phosphorus - fatigue,** Quercus Glandium Spiritus - malaise,** Carduus Marianus – low appetite,** Chelidonium Majus – abdominal pain,** Lappa Major - acne,** Taraxacum Officinale – headache**

**Claims based on traditional homeopathic practice, not accepted medical evidence. Not FDA evaluated.

USES:

May temporarily relieve: • abdominal bloating and soreness • constipation alternating with diarrhea**

**Claims based on traditional homeopathic practice, not accepted medical evidence. Not FDA evaluated.

WARNINGS:

Stop use and ask a doctor if symptoms persist for more than 2 days.

If pregnant or breast-feeding, ask a health professional before use.

Keep out of reach of children. In case of overdose, get medical help or contact a Poison Control Center right away.

DO NOT USE IF TAMPER EVIDENT SEAL IS BROKEN OR MISSING

Store in a cool, dry place.

KEEP OUT OF REACH OF CHILDREN:

In case of overdose, get medical help or contact a Poison Control Center right away.

DIRECTIONS:

• Adults and children 5 to 10 drops orally, 3 times daily or as otherwise directed by a health care professional.

• Consult a physician for use in children under 12 years of age.

INACTIVE INGREDIENTS:

Demineralized water, 20% Ethanol.

QUESTIONS:

Dist. by Energique, Inc.

201 Apple Blvd

Woodbine, IA 51579

800-869-8078

PACKAGE LABEL DISPLAY:

ENERGIQUE

SINCE 1987

HOMEOPATHIC REMEDY

HEPAPAR

1 fl. oz. (30 ml)